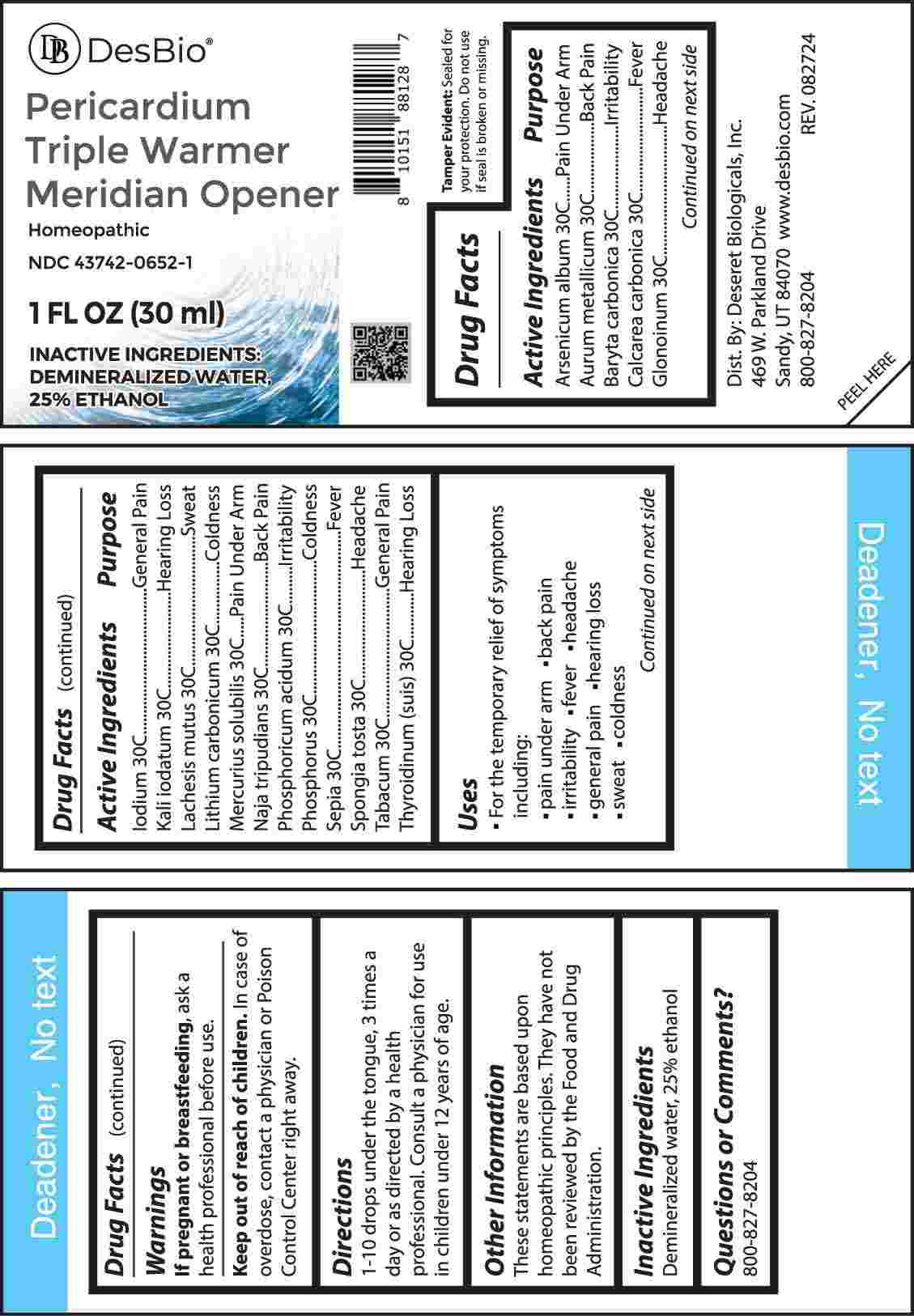 DRUG LABEL: Pericardium Triple Warmer
NDC: 43742-0652 | Form: LIQUID
Manufacturer: Deseret Biologicals, Inc.
Category: homeopathic | Type: HUMAN OTC DRUG LABEL
Date: 20241022

ACTIVE INGREDIENTS: ARSENIC TRIOXIDE 30 [hp_C]/1 mL; GOLD 30 [hp_C]/1 mL; BARIUM CARBONATE 30 [hp_C]/1 mL; OYSTER SHELL CALCIUM CARBONATE, CRUDE 30 [hp_C]/1 mL; NITROGLYCERIN 30 [hp_C]/1 mL; IODINE 30 [hp_C]/1 mL; POTASSIUM IODIDE 30 [hp_C]/1 mL; LACHESIS MUTA VENOM 30 [hp_C]/1 mL; LITHIUM CARBONATE 30 [hp_C]/1 mL; MERCURIUS SOLUBILIS 30 [hp_C]/1 mL; NAJA NAJA VENOM 30 [hp_C]/1 mL; PHOSPHORIC ACID 30 [hp_C]/1 mL; PHOSPHORUS 30 [hp_C]/1 mL; SEPIA OFFICINALIS JUICE 30 [hp_C]/1 mL; SPONGIA OFFICINALIS SKELETON, ROASTED 30 [hp_C]/1 mL; TOBACCO LEAF 30 [hp_C]/1 mL; THYROID 30 [hp_C]/1 mL
INACTIVE INGREDIENTS: WATER; ALCOHOL

DRUG FACTS:

ACTIVE INGREDIENTS:

Arsenicum Album 30C, Aurum Metallicum 30C, Baryta Carbonica 30C, Calcarea Carbonica 30C, Glonoinum 30C, Iodium 30C, Kali Iodatum 30C, Lachesis Mutus 30C, Lithium Carbonicum 30C, Mercurius Solubilis 30C, Naja Tripudians 30C, Phosphoricum Acidum 30C, Phosphorus 30C, Sepia 30C, Spongia Tosta 30C, Tabacum 30C, Thyroidinum (Suis) 30C.

PURPOSE:

Arsenicum Album – Pain Under Arm, Aurum Metallicum – Back Pain, Baryta Carbonica - Irritability, Calcarea Carbonica - Fever, Glonoinum - Headache, Iodium – General Pain, Kali Iodatum – Hearing Loss, Lachesis Mutus - Sweat, Lithium Carbonicum - Coldness, Mercurius Solubilis – Pain Under Arm, Naja Tripudians – Back Pain, Phosphoricum Acidum - Irritability, Phosphorus - Coldness, Sepia - Fever, Spongia Tosta - Headache, Tabacum – General Pain, Thyroidinum (Suis) – Hearing Loss

USES:

• For the temporary relief of symptoms including:

• pain under arm • back pain • irritability • fever • headache

• general pain • hearing loss • sweat • coldness

These statements are based upon homeopathic principles. They have not been reviewed by the Food and Drug Administration.

WARNINGS:

If pregnant of breast-feeding, ask a health professional before use.

Keep out of reach of children. In case of overdose, contact a physician or Poison Control Center right away.

Tamper Evident: Sealed for your protection. Do not use if seal is broken or missing.

KEEP OUT OF REACH OF CHILDREN:

In case of overdose, contact a physician or Poison Control Center right away.

DIRECTIONS:

1-10 drops under the tongue, 3 times a day or as directed by a health professional. Consult a physician for use in children under 12 years of age.

INACTIVE INGREDIENTS:

Demineralized water, 25% Ethanol

QUESTIONS:

Dist. By: Deseret Biologicals, Inc.
469 W. Parkland Drive
Sandy, UT 84070
www.desbio.com

800-827-8204

PACKAGE LABEL DISPLAY:

DesBio

Pericardium

Triple Warmer

Meridian Opener

Homeopathic

NDC 43742-0652-1

1 FL OZ (30 ml)